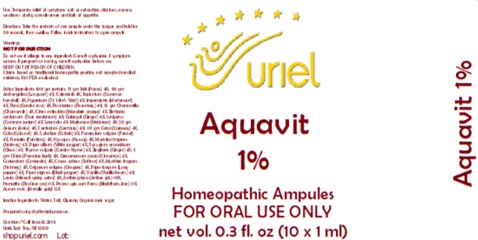 DRUG LABEL: Aquavit 1
NDC: 48951-1065 | Form: LIQUID
Manufacturer: Uriel Pharmacy Inc.
Category: homeopathic | Type: HUMAN OTC DRUG LABEL
Date: 20260202

ACTIVE INGREDIENTS: HONEY 4 [hp_X]/1 mL; ANGELICA ARCHANGELICA ROOT 4 [hp_X]/1 mL; CALENDULA OFFICINALIS FLOWERING TOP 4 [hp_X]/1 mL; EQUISETUM ARVENSE TOP 4 [hp_X]/1 mL; ST. JOHN'S WORT 4 [hp_X]/1 mL; IMPERATORIA OSTRUTHIA ROOT 4 [hp_X]/1 mL; ROSA RUGOSA FLOWER 4 [hp_X]/1 mL; ROSMARINUS OFFICINALIS FLOWERING TOP 4 [hp_X]/1 mL; CHAMOMILE 4 [hp_X]/1 mL; TANGERINE 4 [hp_X]/1 mL; CARDAMOM 4 [hp_X]/1 mL; LESSER GALANGAL ROOT 4 [hp_X]/1 mL; JUNIPER BERRY 4 [hp_X]/1 mL; CENTAURIUM ERYTHRAEA FLOWERING TOP 4 [hp_X]/1 mL; LAVANDULA ANGUSTIFOLIA FLOWER 4 [hp_X]/1 mL; SWEET MARJORAM 4 [hp_X]/1 mL; ANISE 4 [hp_X]/1 mL; CARAWAY SEED 4 [hp_X]/1 mL; COLA NUT 4 [hp_X]/1 mL; LITSEA CUBEBA FRUIT 4 [hp_X]/1 mL; FENNEL SEED 4 [hp_X]/1 mL; FUMARIA OFFICINALIS FLOWERING TOP 4 [hp_X]/1 mL; HYSSOPUS OFFICINALIS WHOLE 4 [hp_X]/1 mL; MYRISTICA FRAGRANS WHOLE 4 [hp_X]/1 mL; BLACK PEPPER 4 [hp_X]/1 mL; SYZYGIUM AROMATICUM FRUIT 4 [hp_X]/1 mL; THYME 4 [hp_X]/1 mL; GINGER 4 [hp_X]/1 mL; QUILLAJA SAPONARIA BARK 4 [hp_X]/1 mL; CINNAMON 4 [hp_X]/1 mL; CORIANDER OIL 4 [hp_X]/1 mL; SAFFRON 4 [hp_X]/1 mL; OREGANO 4 [hp_X]/1 mL; LONG PEPPER 4 [hp_X]/1 mL; VANILLA 4 [hp_X]/1 mL; FERROUS ARSENATE 8 [hp_X]/1 mL; AMBERGRIS 10 [hp_X]/1 mL; FERRIC OXIDE RED 11 [hp_X]/1 mL; PRUNUS SPINOSA FLOWER BUD 11 [hp_X]/1 mL; GOLD 12 [hp_X]/1 mL
INACTIVE INGREDIENTS: WATER; SODIUM CHLORIDE; GLYCERIN; SUCROSE

Aquavit 1

PURPOSE

Use: Temporary relief of symptoms such as exhaustion, dizziness, nausea, weakness during convalescence and lack of appetite.

INDICATIONS AND USAGE

FOR ORAL USE ONLY

DOSAGE AND ADMINISTRATION

Directions: Take the contents of one ampule under the tongue and hold for 30 seconds, then swallow. Follow inside instrucitons to open ampule.

Warnings:
Do not use if allergic to any ingredient. Consult a physician if symptoms worsen. If pregnant or nursing, consult a physician before use.
KEEP OUT OF REACH OF CHILDREN.
Claims based on traditional homeopathic practice, not accepted medical evidence. Not FDA evaluated.

KEEP OUT OF REACH OF CHILDREN.

ACTIVE INGREDIENT

Active Ingredients: 100 gm contains: 75 gm Mel (Honey) 4X; 50 gm Archangelica (Longwort) 4X, Calendula 4X, Equisetum (Common horsetail) 4X, Hypericum (St. John’s Wort) 4X, Imperatoria (Masterwort) 4X, Rosa (Garden rose) 4X, Rosmarinus (Rosemary) 4X; 25 gm Chamomilla (Chamomile) 4X, Citrus reticulata (Mandarin orange) 4X, Elettaria cardamum (True cardamom) 4X, Galangal (Ginger) 4X, Juniperus (Common juniper) 4X, Lavender 4X, Marjorana (Marjoram) 4X; 20 gm Anisum (Anise) 4X, Centurium (Centaury) 4X; 10 gm Carvi (Caraway) 4X, Cola (Cola nut) 4X, Cubebae (Cubeb) 4X, Foeniculum vulgare (Fennel) 4X, Fumaria (Fumitory) 4X, Hyssopus (Hyssop) 4X, Myristica fragrans (Nutmeg) 4X, Piper album (White pepper) 4X, Syzygium aromaticum (Clove) 4X, Thymus vulgaris (Garden thyme) 4X, Zingiberis (Ginger) 4X; 5 gm China (Peruvian bark) 4X, Cinnamomum cassia (Cinnamon) 4X, Coriandrum (Coriander) 4X, Crocus sativus (Saffron) 4X, Myristica fragrans (Nutmeg) 4X, Origanum vulgare (Oregano) 4X, Piper longum (Long pepper) 4X, Piper nigrum (Black pepper) 4X, Vanilla (Vanilla beans) 4X; Levico (Mineral spring water) 8X, Ambra grisea (Amber gris) 10X, Hematite (Red iron ore) 11X, Prunus spin. cum Ferro (Blackthorn, Iron) 11X, Aurum met. (Metallic gold) 12X

Inactive Ingredients: Water, Salt, Glycerin, Organic cane sugar

Prepared using rhythmical processes

QUESTIONS

Questions? Call 866.642.2858 Uriel, East Troy, WI 53120 shopuriel.com Lot: